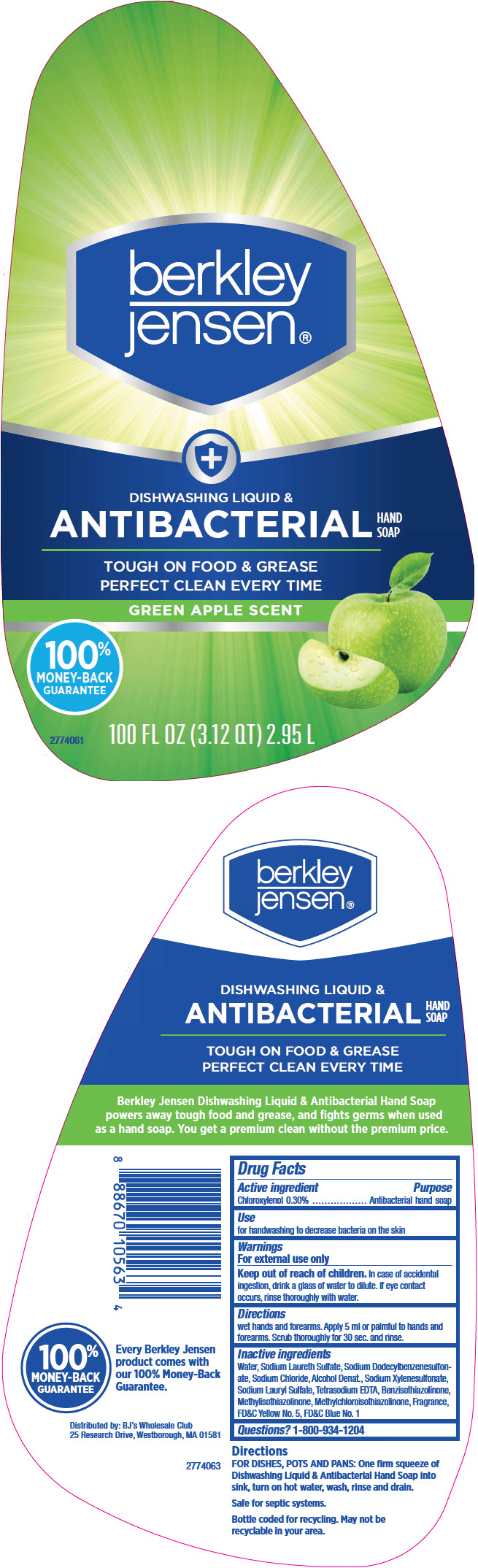 DRUG LABEL: Berkley Jensen Dishwashing and Antibacterial Hand 
NDC: 69560-012 | Form: SOLUTION
Manufacturer: MID-CONTINENT PACKAGING, INC.
Category: otc | Type: HUMAN OTC DRUG LABEL
Date: 20210526

ACTIVE INGREDIENTS: Chloroxylenol 0.3 g/100 mL
INACTIVE INGREDIENTS: Water; Sodium Laureth-3 Sulfate; Sodium Dodecylbenzenesulfonate; Sodium Chloride; Alcohol; Sodium Xylenesulfonate; Sodium Lauryl Sulfate; Edetate Sodium; BENZISOTHIAZOLINONE; METHYLISOTHIAZOLINONE; METHYLCHLOROISOTHIAZOLINONE; FD&C YELLOW NO. 5; FD&C BLUE NO. 1

Berkley Jensen® Dishwashing Liquid & Antibacterial Hand Soap
Green Apple Scent

Drug Facts

Active ingredient

Choroxylenol 0.30%

Purpose

Antibacterial hand soap

Use

for handwashing to decrease bacteria on the skin

Warnings

For external use only

Keep out of reach of children. In case of accidental Ingestion, drink a glass of water to dilute. If eye contact occurs, rinse thoroughly with water.

Directions

wet hands and forearms. Apply 5 ml or palmful to hands and forearms. Scrub thoroughly for 30 sec. and rinse.

Inactive ingredients

Water, Sodium Laureth Sulfate, Sodium Dodecylbenzenesulfon-ate, Sodium Chloride, Alcohol Denat., Sodium Xylenesulfonate, Sodium Lauryl Sulfate, Tetrasodium EDTA, Benzisothiazolinone, Methylisothiazolinone, Methylchloroisothiazolinone, Fragrance, FD&C Yellow No. 5, FD&C Blue No. 1

Questions?

1-800-934-1204

Distributed by: BJ's Wholesale Club
25 Research Drive, Westborough, MA 01581

PRINCIPAL DISPLAY PANEL - 2.95 L Bottle Label

berkley
jensen®

+
DISHWASHING LIQUID &
ANTIBACTERIAL
HAND
SOAP

TOUGH ON FOOD & GREASE
PERFECT CLEAN EVERY TIME

GREEN APPLE SCENT

100%
MONEY-BACK
GUARANTEE

100 FL OZ (3.12 QT) 2.95 L

2774061